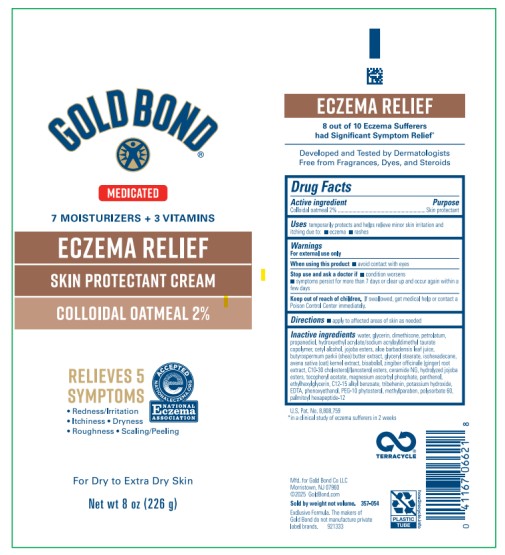 DRUG LABEL: Gold Bond Eczema Relief Medicated Skin Protectant Cream
NDC: 84714-0669 | Form: CREAM
Manufacturer: Gold Bond Co LLC
Category: otc | Type: HUMAN OTC DRUG LABEL
Date: 20251204

ACTIVE INGREDIENTS: OATMEAL 2 g/100 g
INACTIVE INGREDIENTS: WATER; GLYCERIN; DIMETHICONE; PETROLATUM; PROPANEDIOL; HYDROXYETHYL ACRYLATE/SODIUM ACRYLOYLDIMETHYL TAURATE COPOLYMER (100000 MPA.S AT 1.5%); JOJOBA OIL, RANDOMIZED; CETYL ALCOHOL; ALOE VERA LEAF; GLYCERYL STEARATE; BUTYROSPERMUM PARKII (SHEA) BUTTER; ISOHEXADECANE; OAT; LEVOMENOL; GINGER; C10-30 CHOLESTEROL/LANOSTEROL ESTERS; CERAMIDE NG; HYDROLYZED JOJOBA ESTERS (ACID FORM); ALPHA-TOCOPHEROL ACETATE; MAGNESIUM ASCORBYL PHOSPHATE; PANTHENOL; ETHYLHEXYLGLYCERIN; ALKYL (C12-15) BENZOATE; TRIBEHENIN; POTASSIUM HYDROXIDE; EDETIC ACID; PHENOXYETHANOL; METHYLPARABEN; POLYSORBATE 60; PALMITOYL HEXAPEPTIDE-12

Gold Bond Medicated Eczema Relief Cream

Gold Bond Eczema Relief Medicated Skin Protectant Cream

Drug Facts

Active ingredient

Colloidal oatmeal 2%

Purpose

Skin protectant

Uses

temporarily protects and helps relieve minor skin irritation and itching due to:

- eczema
- rashes

Warnings

For external use only

When using this product

- avoid contact with eyes

Stop use and ask a doctor if

- condition worsens
- symptoms persist for more than 7 days or clear up and occur again within a few days

Keep out of reach of children.

If swallowed, get medical help or contact a Poison Control Center immediately.

Directions

- apply to affected areas of skin as needed

Inactive ingredients

water, glycerin, dimethicone, petrolatum, propanediol, hydroxyethyl acrylate/sodium acryloyldimethyl taurate copolymer, jojoba esters, cetyl alcohol, aloe barbadensis leaf juice, glyceryl stearate, butyrospermum parkii (shea) butter extract, isohexadecane, avena sativa (oat) kernel extract, bisabolol, zingiber officinale (ginger) root extract, C10-30 cholesterol/lanosterol esters, ceramide NG, hydrolyzed jojoba esters, tocopheryl acetate, magnesium ascorbyl phosphate, panthenol, ethylhexylglycerin, C12-15 alkyl benzoate, tribehenin, potassium hydroxide, EDTA, phenoxyethanol, PEG-10 phytosterol, methylparaben, polysorbate 60, palmitoyl hexapeptide-12

PRINCIPAL DISPLAY PANEL

Gold Bond Eczema Relief Medicated Skin Protectant Cream
Net wt 8 oz (226 g)